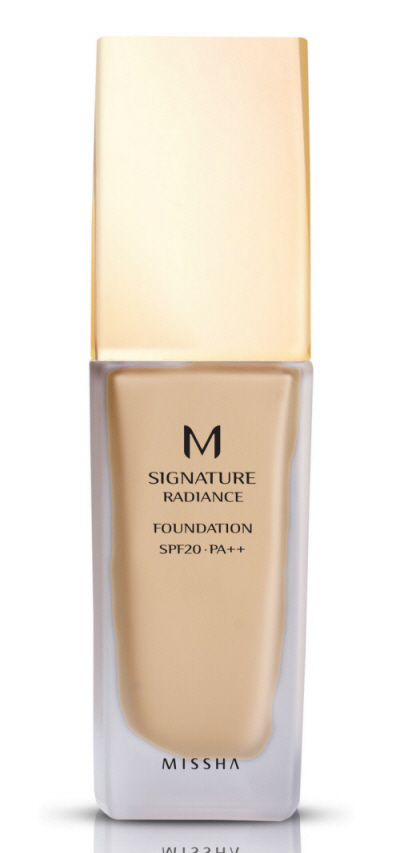 DRUG LABEL: MISSHA M SIGNATURE RADIANCE FOUNDATION
NDC: 13733-004 | Form: CREAM
Manufacturer: ABLE C&C CO., LTD.
Category: otc | Type: HUMAN OTC DRUG LABEL
Date: 20100519

ACTIVE INGREDIENTS: TITANIUM DIOXIDE 3.25 mL/35 mL

Drug Facts

Active Ingredient: TITANIUM DIOXIDE

Inactive Ingredients:
Water, Cyclopentasiloxane, Trimethylsiloxysilicate, Butylene Glycol, Glycerin, PEG-10 Dimethicone, Calcium Cerium Oxide, Iron Oxides, Neopentyl Glycol Diethylhexanoate, Tribehenin, Magnesium Sulfate, Disteardimonium Hectorite, Mica, Sorbitan Sesquioleate, Tocopheryl Acetate, Phenyl Trimethicone, Polymethylsilsesquioxane, PEG/PPG-18/18 Dimethicone, Methylparaben, Chlorphenesin, Triethoxycaprylylsilane, Aluminum Hydroxide, Stearic Acid, Propylparaben, Fragrance, Fullerenes, PVP, Diamond powder, Montmorillonite, Haematococcus Pluvialis Extract, Methyl Methacrylate Crosspolymer, Hydrolyzed Extensin, Astaxanthin, Prunus Amygdalus Dulcis (Sweet Almond) Seed Extract, Amethyst Powder, Pearl Powder, Tourmaline, Sodium Methylparaben, Sodium Propylparaben, Platinum Powder, Polysorbate 80, Sodium Ethylparaben

DESCRIPTION

Directions: After basic skin care, apply an appropriate amount along the skin texture and finish with powder. Do not need to apply Sun cream in addition.
Caution: For external use only. Do not swallow. Keep out of reach of children. Avoid contact with eyes.